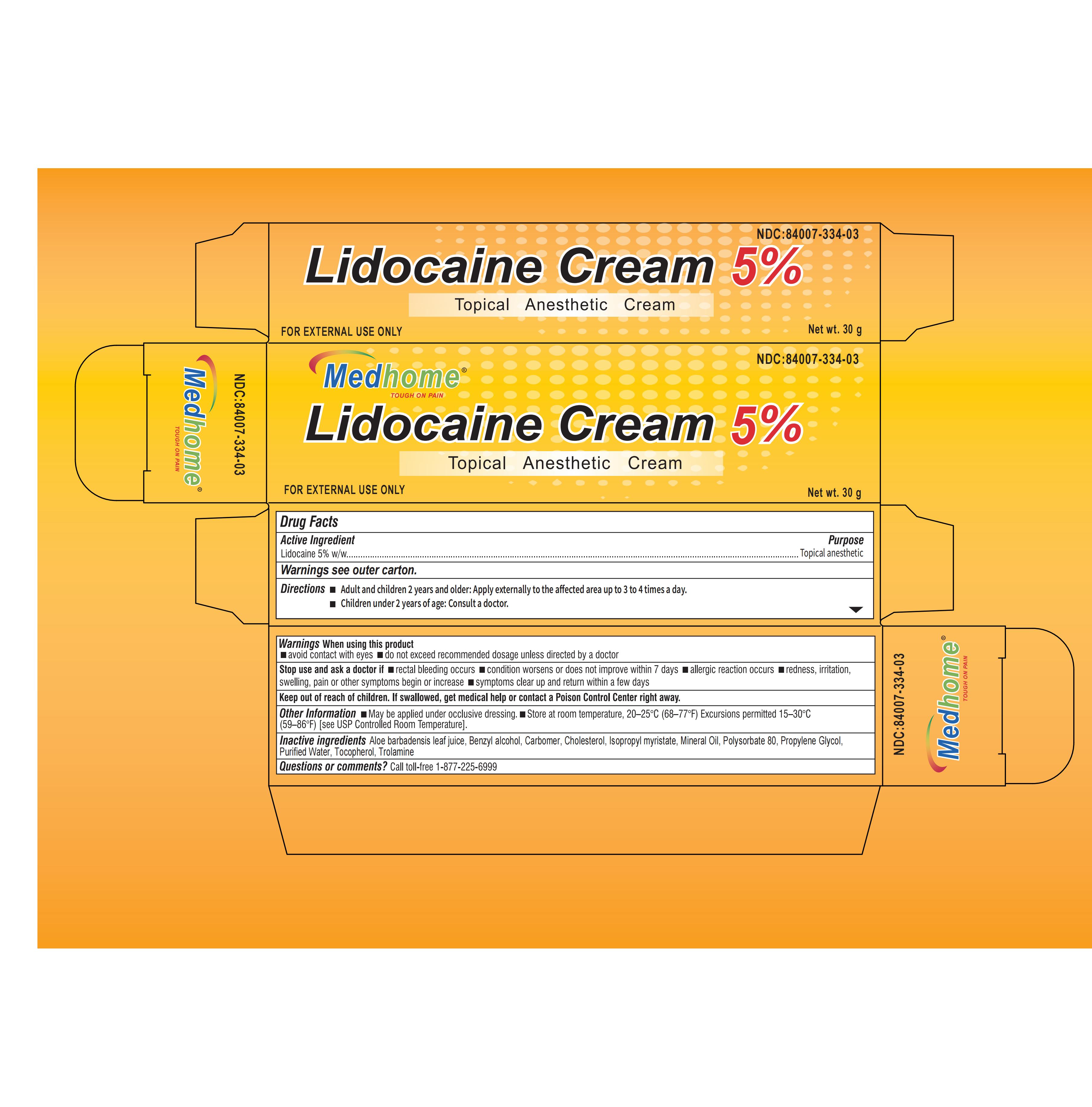 DRUG LABEL: LIDOCAINE 5%
NDC: 84007-335 | Form: CREAM
Manufacturer: Medhome Pharma Inc
Category: otc | Type: HUMAN OTC DRUG LABEL
Date: 20251222

ACTIVE INGREDIENTS: LIDOCAINE 5 g/100 g
INACTIVE INGREDIENTS: ALOE BARBADENSIS LEAF JUICE; TROLAMINE; TOCOPHEROL; CHOLESTEROL; WATER; CARBOMER 934; ISOPROPYL MYRISTATE; POLYSORBATE 80; PROPYLENE GLYCOL; BENZYL ALCOHOL; MINERAL OIL

Active Ingredient

Lidocaine 5%

Purpose

Topical anesthetic

USE

For temporary relief of local discomfort, itching, pain, soreness, or burning related to the tattoo process

Warnings

For external use only.

Do not use

Do not exceed the recommended daily dosage unless directed by a doctor

Stop Use

Do not exceed the recommended daily dosage unless directed by a doctor.

Avoid contact with eyes. lf this happens, rinse thoroughly with water.

lf symptoms persist for more than 7 days or subside but occur again within 3 days, stop use and consult a physician.

Stop use and seek medical attention if signs of an allergy occur, such as redness,iritation, sweling, pain, or other severe symptoms. fsymptoms do not subside completely within 7 days, seek medica help.

Ask Doctor

Stop use and sek meditcal attention if signs of an alerqy occur,such as rednes,irtation,sweling, pain, or other severe symptoms.If symptoms do not subside completely within 7 days, seek medical help.

Directions

Before applying the numbing cream, thoroughly wash your hands and wear disposable tattoo gloves.

Clean the area of the body receivina the tattoo,Dry completely.

Apply a generous amount of numbing cream to the cleaned area and rub it inthoroughly in a circlar motion for30 to 60 seconds,Then. cover with plastic wrap.

Leave the cream and wrap in place for 30 to 45 minutes,Wipe away the cream and thoroughly clean the area to prepare for a pain-free tattoo.

Keep Out Of Reach Of Children

Other information

Store between 15-30℃(59-86F). Avoid freezing and excessive heat above 40 ℃(104°F).

Inactive ingredients

Water,Carbomer934, propylene Glycol,soybean Lecithin,.Alpha.-Tocopherol Acetate,Benzyl Alcohol.